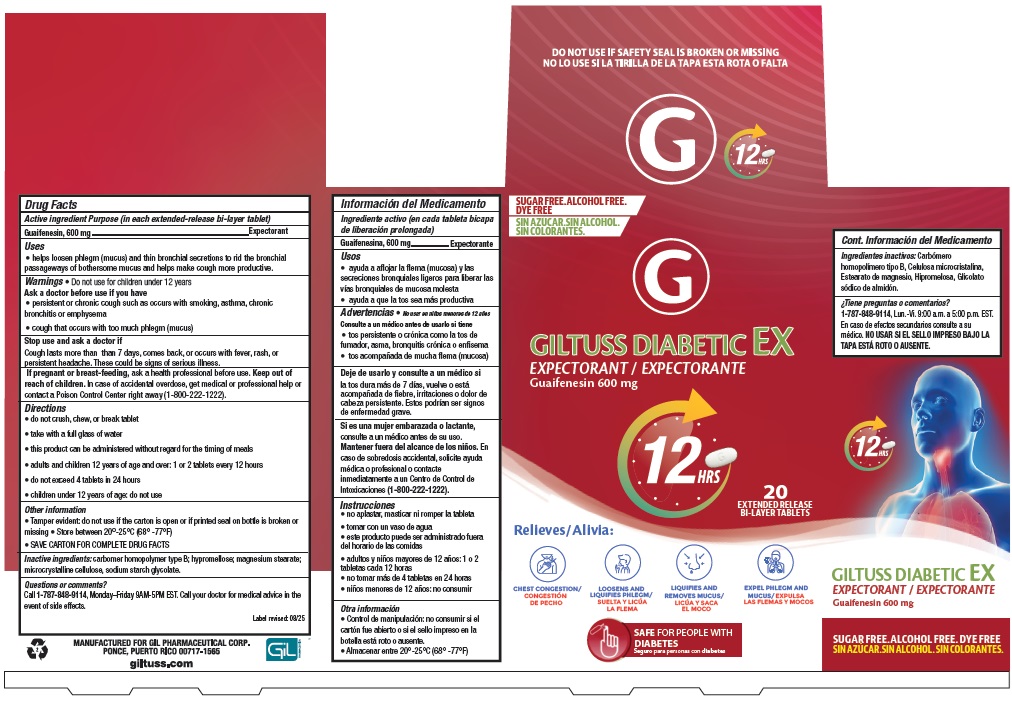 DRUG LABEL: GILTUSS DIABETIC EX
NDC: 58552-339 | Form: TABLET
Manufacturer: Gil Pharmaceutical Corp
Category: otc | Type: HUMAN OTC DRUG LABEL
Date: 20251009

ACTIVE INGREDIENTS: GUAIFENESIN 600 mg/1 1
INACTIVE INGREDIENTS: CARBOMER HOMOPOLYMER TYPE B (ALLYL SUCROSE CROSSLINKED); HYPROMELLOSE, UNSPECIFIED; MAGNESIUM STEARATE; MICROCRYSTALLINE CELLULOSE; SODIUM STARCH GLYCOLATE TYPE A

GILTUSS DIABETIC EX
EXPECTORANT / EXPECTORANTE
Guaifenesin 600 mg

Active ingredient Purpose (in each extended-release bi-layer tablet)

Guaifenesin, 600 mg....................................................................Expectorant

Uses

- helps loosen phlegm (mucus) and thin bronchial secretions to rid the bronchial passageways of bothersome mucus and helps make cough more productive.

Warnings

- Do not use for children under 12 years

Ask a doctor before use if you have

- persistent or chronic cough such as occurs with smoking, asthma, chronic bronchitis or emphysema
- cough that occurs with too much phlegm (mucus)

Stop use and ask a doctor if

Cough lasts more than than 7 days, comes back, or occurs with fever, rash, or persistent headache. These could be signs of serious illness.

PREGNANCY OR BREAST FEEDING

If pregnant or breast-feeding, ask a health professional before use.

Keep out of reach of children. In case of accidental overdose, get medical or professional help or contact a Poison Control Center right away (1-800-222-1222).

Directions

- do not crush, chew, or break tablet
- take with a full glass of water
- this product can be administered without regard for the timing of meals
- adults and children 12 years of age and over: 1 or 2 tablets every 12 hours
- do not exceed 4 tablets in 24 hours
- children under 12 years of age: do not use

Other information

- Tamper evident: do not use if the carton is open or if printed seal on bottle is broken or missing
- Store between 20°-25°C (68° -77°F)
- SAVE CARTON FOR COMPLETE DRUG FACTS

INACTIVE INGREDIENT

Inactive ingredients:carbomer homopolymer type B; hypromellose; magnesium stearate; microcrystalline cellulose, sodium starch glycolate.

Questions or comments?

Call 1-787-848-9114, Monday–Friday 9AM-5PM EST. Call your doctor for medical advice in the event of side effects.

revised: 08/25

PRINCIPAL DISPLAY PANEL

GILTUSS DIABETIC EX EXPECTORANT / EXPECTORANTE (Guaifenesin 600 mg) - NDC 58552-339-20 - 20 Tabs Bottle label